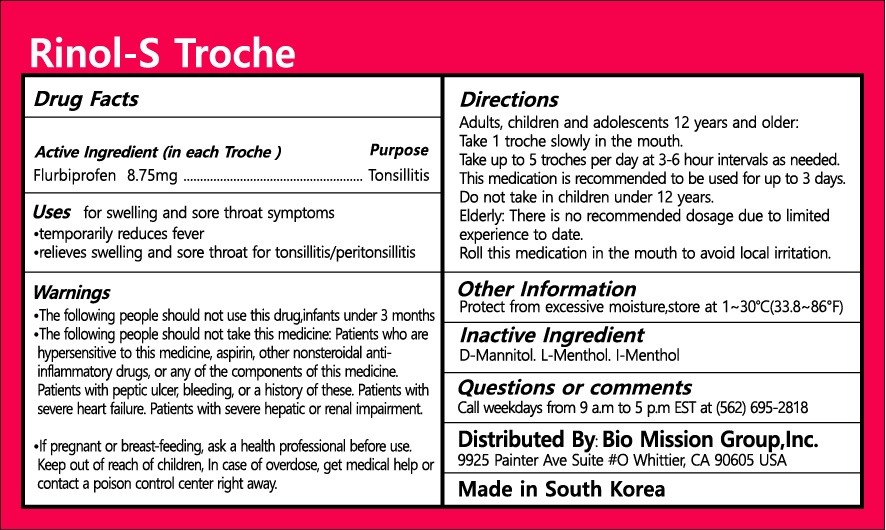 DRUG LABEL: Rinol-STroche
NDC: 72988-0041 | Form: TROCHE
Manufacturer: Lydia Co., Ltd.
Category: otc | Type: HUMAN OTC DRUG LABEL
Date: 20241031

ACTIVE INGREDIENTS: FLURBIPROFEN 8.75 mg/1 1
INACTIVE INGREDIENTS: MANNITOL; LEVOMENTHOL

ACTIVE INGREDIENT

flurbiprofen

PURPOSE

for swelling and sore throat symptoms, temporarily reduces feber, relieves swelling and sore throat for tonsillitis/peritonsillitis

Keep out of reach of children

INDICATIONS AND USAGE

please see attached Drug Facts

WARNINGS

please see attached Drug Facts

INACTIVE INGREDIENT

d-mannitil, l-menthol, L-menthol

DOSAGE AND ADMINISTRATION

oral use only